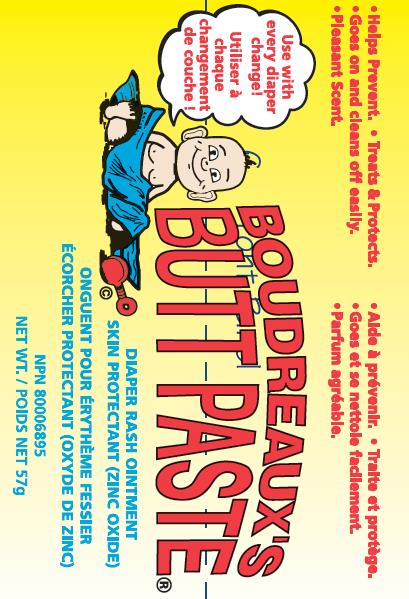 DRUG LABEL: Boudreauxs
NDC: 0132-0557 | Form: CREAM
Manufacturer: C.B. Fleet Company, Inc.
Category: otc | Type: HUMAN OTC DRUG LABEL
Date: 20160328

ACTIVE INGREDIENTS: ZINC OXIDE 16 g/113 g
INACTIVE INGREDIENTS: CASTOR OIL; MINERAL OIL; PARAFFIN; BALSAM PERU; PETROLATUM

Active Ingredient

Zinc Oxide, 16%........Skin Protectant

Warnings

- For external use only.
- When using this product avoid contact with the eyes.

Stop use and ask a doctor if

Condition worsens or does not improve after 7 days.

Warnings

Keep out of the reach of children.

Warnings

If swallowed, seek medical help or call Poison Control Center immediately.

Inactive Ingredients

Castor Oil, Mineral Oil, Paraffin, Peruvian Balsam, Petrolatum

Uses

- Helps treat and prevent diaper rash
- Protects chafed skin due to diaper rash and helps seal out wetness

Other Information

- Store at room temperature, 20C to 27C (68F to 80F).
- Use with infants, children and adults.
- Will stain clothing and fabric.

Directions for Use

- Change wet and soiled diaper immediately.
- Cleanse the diaper area and allow to dry.
- Apply ointment liberally and as often as necessary with each diaper change and especially when exposed to wet diapers for a prolonged period of time, such as bedtime.

Questions?

Call toll free 1-855-785-2888